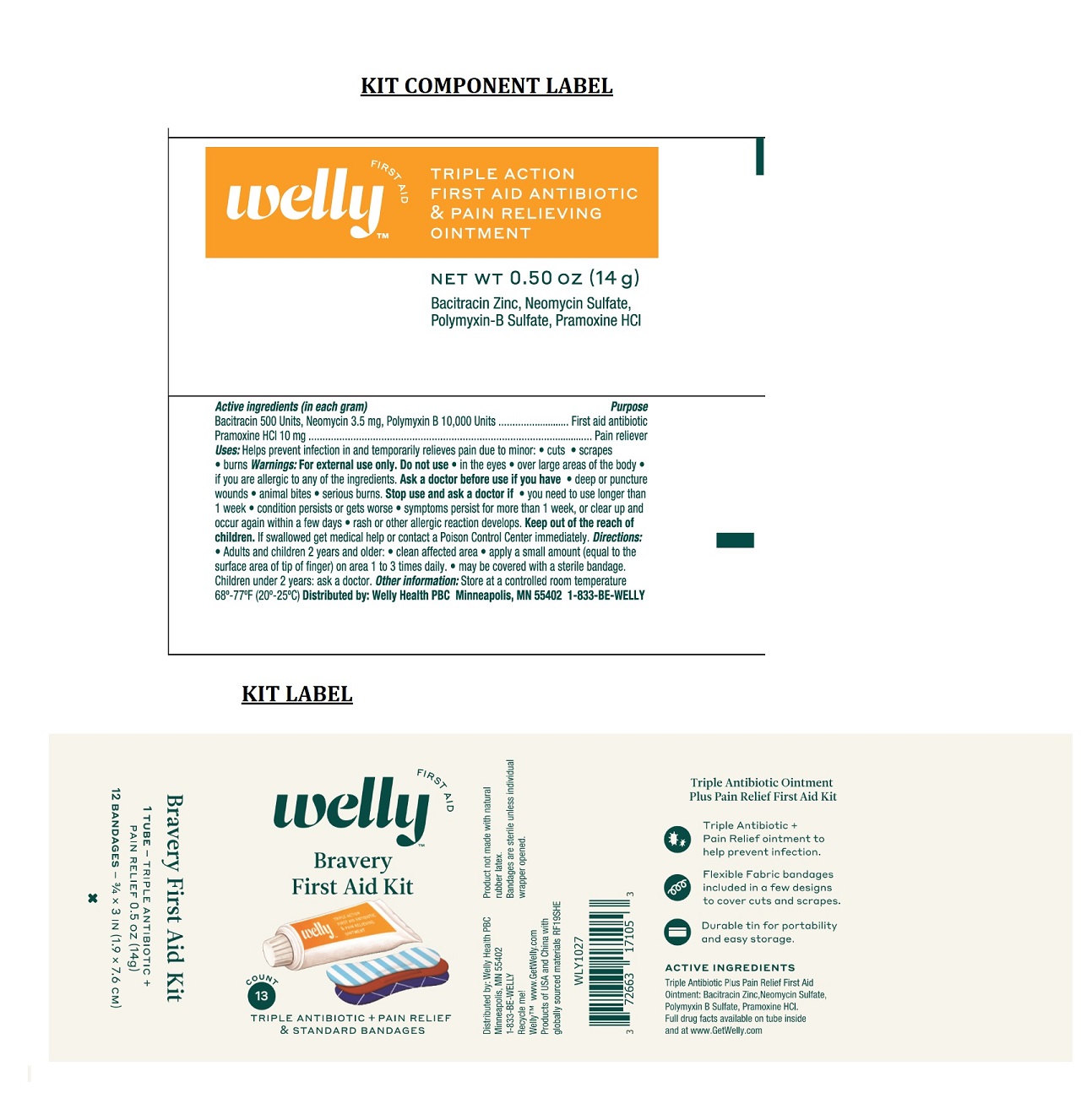 DRUG LABEL: Welly Bravery First Aid Kit
NDC: 72663-171 | Form: KIT | Route: TOPICAL
Manufacturer: Welly Health PBC
Category: otc | Type: HUMAN OTC DRUG LABEL
Date: 20211231

ACTIVE INGREDIENTS: BACITRACIN ZINC 500 [USP'U]/1 g; NEOMYCIN SULFATE 3.5 mg/1 g; POLYMYXIN B SULFATE 10000 [USP'U]/1 g; PRAMOXINE HYDROCHLORIDE 10 mg/1 g
INACTIVE INGREDIENTS: PETROLATUM

Welly Bravery First Aid Kit

Active ingredients (in each gram)

Bacitracin Zinc 500 Units

Neomycin Sulfate 3.5 mg

Polymyxin B Sulfate 10,000 Units

Pramoxine Hydrochloride 10 mg

Purpose

First aid antibiotic

First aid antibiotic

First aid antibiotic

Pain reliever

Uses:

Helps prevent infection in and temporarily relieves pain due to minor: • cuts • scrapes • burns

Warnings:

For external use only.

Do not use • in the eyes • over large areas of the body • if you are allergic to any of the ingredients.

Ask a doctor before use if you have • deep or puncture wounds • animal bites • serious burns.

Stop use and ask a doctor if • you need to use longer than 1 week • condition persists or gets worse • symptoms persist for more than 1 week, or clear up and occur again within a few days • rash or other allergic reaction develops.

KEEP OUT OF REACH OF CHILDREN

Keep out of the reach of children. If swallowed get medical help or contact a Poison Control Center immediately.

Directions:

• Adults and children 2 years and older: • clean affected area • apply a small amount (equal to the surface area of tip of finger) on area 1 to 3 times daily. • may be covered with a sterile bandage.
• Children under 2 years: ask a doctor.

Other information:

Store at a controlled room temperature 68°-77°F (20°-25°C)

Inactive Ingredient:

Petrolatum

Questions? 1-833-BE-WELLY

TRIPLE ANTIBIOTIC + PAIN RELIEF & STANDARD BANDAGES

Triple Antibiotic Ointment Plus Pain Relief First Aid Kit

- Triple Antibiotic + Pain relief ointment to help prevent infection.
- Flexible Fabric bandages included in a few designs to cover cuts and scrapes.
- Durable tin for portability and easy storage.

Product not made with natural rubber latex.
Bandages are sterile unless individual wrapper opened.

Bravery First Aid Kit

1 TUBE- TRIPLE ANTIBIOTIC + PAIN RELIEF 0.5 OZ (14g)

12 BANDAGES - 3/4 x 3 IN (1.9 x 7.6 CM)

Distributed by: Welly Health PBC
Minneapolis, MN 55402
1-833-BE-WELLY

Recycle me!

WellyTM www.GetWelly.com